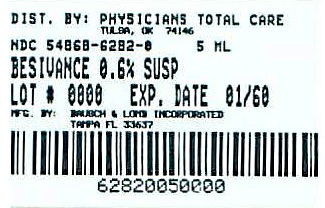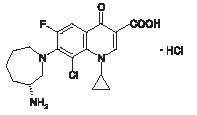 DRUG LABEL: Besivance
NDC: 54868-6282 | Form: SUSPENSION
Manufacturer: Physicians Total Care, Inc.
Category: prescription | Type: HUMAN PRESCRIPTION DRUG LABEL
Date: 20090401

ACTIVE INGREDIENTS: BESIFLOXACIN 6 mg/1 mL
INACTIVE INGREDIENTS: BENZALKONIUM CHLORIDE; POLYCARBOPHIL; MANNITOL; POLOXAMER 407; SODIUM CHLORIDE; EDETATE DISODIUM; SODIUM HYDROXIDE; WATER

HIGHLIGHTS OF PRESCRIBING INFORMATION

These highlights do not include all the information needed to use Besivance safely and effectively. See full prescribing information for Besivance.
BesivanceTM (besifloxacin ophthalmic suspension) 0.6%
Sterile topical ophthalmic drops
Initial U.S. Approval: 2009

1 INDICATIONS AND USAGE

Besivance™ (besifloxacin ophthalmic suspension) 0.6%, is a quinolone antimicrobial indicated for the treatment of bacterial conjunctivitis caused by susceptible isolates of the following bacteria:

CDC coryneform group G

Corynebacterium pseudodiphtheriticum*, Corynebacterium striatum*, Haemophilus influenzae, Moraxella lacunata*, Staphylococcus aureus, Staphylococcus epidermidis, Staphylococcus hominis*, Staphylococcus lugdunensis*, Streptococcus mitis group, Streptococcus oralis, Streptococcus pneumoniae, Streptococcus salivarius*

*Efficacy for this organism was studied in fewer than 10 infections. (1)

2 DOSAGE AND ADMINISTRATION

Instill one drop in the affected eye(s) 3 times a day, four to twelve hours apart for 7 days. (2)

3 DOSAGE FORMS AND STRENGTHS

7.5 mL size bottle filled with 5 mL of besifloxacin ophthalmic suspension, 0.6% (3)

4 CONTRAINDICATIONS

None

5 WARNINGS AND PRECAUTIONS

Topical Ophthalmic Use Only. (5.1)

Growth of Resistant Organisms with Prolonged Use. (5.2)

Avoidance of Contact Lenses. Patients should not wear contact lenses if they have signs or symptoms of bacterial conjunctivitis or during the course of therapy with Besivance™ (5.3)

6 ADVERSE REACTIONS

The most common adverse event reported in 2% of patients treated with Besivance™ was conjunctival redness. (6)

To report SUSPECTED ADVERSE REACTIONS, contact Bausch & Lomb Incorporated at 1-800-323-0000 or FDA at 1-800-FDA-1088 or www.fda.gov/medwatch

FULL PRESCRIBING INFORMATION

1 INDICATIONS AND USAGE

Besivance™ (besifloxacin ophthalmic suspension) 0.6%, is indicated for the treatment of bacterial conjunctivitis caused by susceptible isolates of the following bacteria:

CDC coryneform group G

Corynebacterium pseudodiphtheriticum*

Corynebacterium striatum*

Haemophilus influenzae

Moraxella lacunata*

Staphylococcus aureus

Staphylococcus epidermidis

Staphylococcus hominis*

Staphylococcus lugdunensis*

Streptococcus mitis group

Streptococcus oralis

Streptococcus pneumoniae

Streptococcus salivarius*

*Efficacy for this organism was studied in fewer than 10 infections.

2 DOSAGE AND ADMINISTRATION

Invert closed bottle and shake once before use.

Instill one drop in the affected eye(s) 3 times a day, four to twelve hours apart for 7 days.

3 DOSAGE FORMS AND STRENGTHS

7.5 mL bottle filled with 5 mL of besifloxacin ophthalmic suspension, 0.6%.

4 CONTRAINDICATIONS

None

5 WARNINGS AND PRECAUTIONS

5.1 Topical Ophthalmic Use Only

NOT FOR INJECTION INTO THE EYE.

Besivance™ is for topical ophthalmic use only, and should not be injected subconjunctivally, nor should it be introduced directly into the anterior chamber of the eye.

5.2 Growth of Resistant Organisms with Prolonged Use

As with other anti-infectives, prolonged use of Besivance™ (besifloxacin ophthalmic suspension) 0.6% may result in overgrowth of non-susceptible organisms, including fungi. If super-infection occurs, discontinue use and institute alternative therapy. Whenever clinical judgment dictates, the patient should be examined with the aid of magnification, such as slit-lamp biomicroscopy, and, where appropriate, fluorescein staining.

5.3 Avoidance of Contact Lenses

Patients should not wear contact lenses if they have signs or symptoms of bacterial conjunctivitis or during the course of therapy with Besivance™.

6 ADVERSE REACTIONS

Because clinical trials are conducted under widely varying conditions, adverse reaction rates observed in one clinical trial of a drug cannot be directly compared with the rates in the clinical trials of the same or another drug and may not reflect the rates observed in practice.

The data described below reflect exposure to Besivance™ in approximately 1,000 patients between 1 and 98 years old with clinical signs and symptoms of bacterial conjunctivitis.

The most frequently reported ocular adverse event was conjunctival redness, reported in approximately 2% of patients.

Other adverse events reported in patients receiving Besivance™ occurring in approximately 1-2% of patients included: blurred vision, eye pain, eye irritation, eye pruritus and headache.

8 USE IN SPECIFIC POPULATIONS

8.1 Pregnancy

Pregnancy Category C. Oral doses of besifloxacin up to 1000 mg/kg/day were not associated with visceral or skeletal malformations in rat pups in a study of embryo-fetal development, although this dose was associated with maternal toxicity (reduced body weight gain and food consumption) and maternal mortality. Increased post-implantation loss, decreased fetal body weights, and decreased fetal ossification were also observed. At this dose, the mean Cmax in the rat dams was approximately 20 mcg/mL, >45,000 times the mean plasma concentrations measured in humans. The No Observed Adverse Effect Level (NOAEL) for this embryo-fetal development study was 100 mg/kg/day (Cmax, 5 mcg/mL, >11,000 times the mean plasma concentrations measured in humans).

In a prenatal and postnatal development study in rats, the NOAELs for both fetal and maternal toxicity were also 100 mg/kg/day. At 1000 mg/kg/day, the pups weighed significantly less than controls and had a reduced neonatal survival rate. Attainment of developmental landmarks and sexual maturation were delayed, although surviving pups from this dose group that were reared to maturity did not demonstrate deficits in behavior, including activity, learning and memory, and their reproductive capacity appeared normal.

Since there are no adequate and well-controlled studies in pregnant women, Besivance™ should be used during pregnancy only if the potential benefit justifies the potential risk to the fetus.

8.3 Nursing Mothers

Besifloxacin has not been measured in human milk, although it can be presumed to be excreted in human milk. Caution should be exercised when Besivance™ is administered to a nursing mother.

8.4 Pediatric Use

The safety and effectiveness of Besivance™ in infants below one year of age have not been established. The efficacy of Besivance™ in treating bacterial conjunctivitis in pediatric patients one year or older has been demonstrated in controlled clinical trials [see 14 CLINICAL STUDIES].

There is no evidence that the ophthalmic administration of quinolones has any effect on weight bearing joints, even though systemic administration of some quinolones has been shown to cause arthropathy in immature animals.

8.5 Geriatric Use

No overall differences in safety and effectiveness have been observed between elderly and younger patients.

11 DESCRIPTION

Besivance™ (besifloxacin ophthalmic suspension) 0.6%, is a sterile ophthalmic suspension of besifloxacin formulated with DuraSite®* (polycarbophil, edetate disodium dihydrate and sodium chloride). Each mL of Besivance™ contains 6.63 mg besifloxacin hydrochloride equivalent to 6 mg besifloxacin base. It is an 8-chloro fluoroquinolone anti-infective for topical ophthalmic use.

C19H21ClFN3O3•HCl

Mol Wt 430.30

Chemical Name: (+)-7-[(3R)-3-aminohexahydro-1H-azepin-1-yl]-8-chloro-1- cyclopropyl-6-fluoro-4-oxo-1,4-dihydroquinoline-3-carboxylic acid hydrochloride.

Besifloxacin hydrochloride is a white to pale yellowish-white powder.

Each mL Contains:

Active: besifloxacin 0.6% (6 mg/mL);

Preservative: benzalkonium chloride 0.01%

Inactives: polycarbophil, mannitol, poloxamer 407, sodium chloride, edetate disodium dihydrate, sodium hydroxide and water for injection.

Besivance™ is an isotonic suspension with an osmolality of approximately 290 mOsm/kg.

12 CLINICAL PHARMACOLOGY

12.1 Mechanism of Action

Besifloxacin is a fluoroquinolone antibacterial [see 12.4 Clinical Pharmacology, Microbiology].

12.3 Pharmacokinetics

Plasma concentrations of besifloxacin were measured in adult patients with suspected bacterial conjunctivitis who received Besivance™ bilaterally three times a day (16 doses total). Following the first and last dose, the maximum plasma besifloxacin concentration in each patient was less than 1.3 ng/mL. The mean besifloxacin Cmax was 0.37 ng/mL on day 1 and 0.43 ng/mL on day 6. The average elimination half-life of besifloxacin in plasma following multiple dosing was estimated to be 7 hours.

12.4 Microbiology

Besifloxacin is an 8-chloro fluoroquinolone with a N-1 cyclopropyl group. The compound has activity against Gram-positive and Gram-negative bacteria due to the inhibition of both bacterial DNA gyrase and topoisomerase IV. DNA gyrase is an essential enzyme required for replication, transcription and repair of bacterial DNA. Topoisomerase IV is an essential enzyme required for partitioning of the chromosomal DNA during bacterial cell division. Besifloxacin is bactericidal with minimum bactericidal concentrations (MBCs) generally within one dilution of the minimum inhibitory concentrations (MICs).

The mechanism of action of fluoroquinolones, including besifloxacin, is different from that of aminoglycoside, macrolide, and β-lactam antibiotics. Therefore, besifloxacin may be active against pathogens that are resistant to these antibiotics and these antibiotics may be active against pathogens that are resistant to besifloxacin. In vitro studies demonstrated crossresistance between besifloxacin and some fluoroquinolones.

In vitro resistance to besifloxacin develops via multiple-step mutations and occurs at a general frequency of < 3.3 x 10^-10 for Staphylococcus aureus and < 7 x 10^-10 for Streptococcus pneumoniae.

Besifloxacin has been shown to be active against most isolates of the following bacteria both in vitro and in conjunctival infections treated in clinical trials as described in the INDICATIONS AND USAGE section:

CDC coryneform group G

Corynebacterium pseudodiphtheriticum*

Corynebacterium striatum*

Haemophilus influenzae

Moraxella lacunata*

Staphylococcus aureus

Staphylococcus epidermidis

Staphylococcus hominis*

Staphylococcus lugdunensis*

Streptococcus mitis group

Streptococcus oralis

Streptococcus pneumoniae

Streptococcus salivarius*

*Efficacy for this organism was studied in fewer than 10 infections.

13 NONCLINICAL TOXICOLOGY

13.1 Carcinogenesis, Mutagenesis, Impairment of Fertility

Long-term studies in animals to determine the carcinogenic potential of besifloxacin have not been performed.

No in vitro mutagenic activity of besifloxacin was observed in an Ames test (up to 3.33 mcg/plate) on bacterial tester strains Salmonella typhimurium TA98, TA100, TA1535, TA1537 and Escherichia coli WP2uvrA. However, it was mutagenic in S. typhimurium strain TA102 and E. coli strain WP2(pKM101). Positive responses in these strains have been observed with other quinolones and are likely related to topoisomerase inhibition.

Besifloxacin induced chromosomal aberrations in CHO cells in vitro and it was positive in an in vivo mouse micronucleus assay at oral doses ≥ 1500 mg/kg. Besifloxacin did not induce unscheduled DNA synthesis in hepatocytes cultured from rats given the test compound up to 2,000 mg/ kg by the oral route. In a fertility and early embryonic development study in rats, besifloxacin did not impair the fertility of male or female rats at oral doses of up to 500 mg/kg/day. This is over 10,000 times higher than the recommended total daily human ophthalmic dose.

14 CLINICAL STUDIES

In a randomized, double-masked, vehicle controlled, multicenter clinical trial, in which patients 1-98 years of age were dosed 3 times a day for 5 days, Besivance™ was superior to its vehicle in patients with bacterial conjunctivitis. Clinical resolution was achieved in 45% (90/198) for the Besivance™ treated group versus 33% (63/191) for the vehicle treated group (difference 12%, 95% CI 3% - 22%). Microbiological outcomes demonstrated a statistically significant eradication rate for causative pathogens of 91% (181/198) for the Besivance™ treated group versus 60% (114/191) for the vehicle treated group (difference 31%, 95% CI 23% - 40%). Microbiologic eradication does not always correlate with clinical outcome in anti-infective trials.

16 HOW SUPPLIED/STORAGE AND HANDLING

Besivance™ (besifloxacin ophthalmic suspension) 0.6%, is supplied as a sterile ophthalmic suspension in a white low density polyethylene (LDPE) bottle with a controlled dropper tip and tan polypropylene cap. Tamper evidence is provided with a shrink band around the cap and neck area of the package.

5 mL in 7.5 mL bottle

NDC 54868-6282-0

Storage: Store at 15°- 25°C (59° - 77°F). Protect from Light.

Invert closed bottle and shake once before use.

Rx Only

17 PATIENT COUNSELING INFORMATION

Patients should be advised to avoid contaminating the applicator tip with material from the eye, fingers or other source.

Although Besivance™ is not intended to be administered systemically, quinolones administered systemically have been associated with hypersensitivity reactions, even following a single dose. Patients should be advised to discontinue use immediately and contact their physician at the first sign of a rash or allergic reaction.

Patients should be told that although it is common to feel better early in the course of the therapy, the medication should be taken exactly as directed. Skipping doses or not completing the full course of therapy may (1) decrease the effectiveness of the immediate treatment and (2) increase the likelihood that bacteria will develop resistance and will not be treatable by Besivance™ or other antibacterial drugs in the future.

Patients should be advised not to wear contact lenses if they have signs or symptoms of bacterial conjunctivitis or during the course of therapy with Besivance™.

Patients should be advised to thoroughly wash hands prior to using Besivance™.

Patients should be instructed to invert closed bottle (upside down) and shake once before each use. Remove cap with bottle still in the inverted position. Tilt head back, and with bottle inverted, gently squeeze bottle to instill one drop into the affected eye(s).

MANUFACTURER INFORMATION

Manufactured by: Bausch & Lomb Incorporated
Tampa, Florida 33637
©Bausch & Lomb Incorporated

U.S. Patent No. 6,685,958
U.S. Patent No. 6,699,492
U.S. Patent No. 5,447,926

Besivance™ is a trademark of Bausch & Lomb Incorporated

*DuraSite is a trademark of InSite Vision Incorporated

April 2009

Relabeling and Repackaging by:
Physicians Total Care, Inc.
Tulsa, OK 74146

PACKAGE/LABEL PRINCIPAL DISPLAY PANEL

NDC 54868-6282-0

Besivance

besifloxacin ophthalmic suspension, 0.6%

Rx only
Sterile

FOR OPHTHALMIC USE ONLY.

5 mL